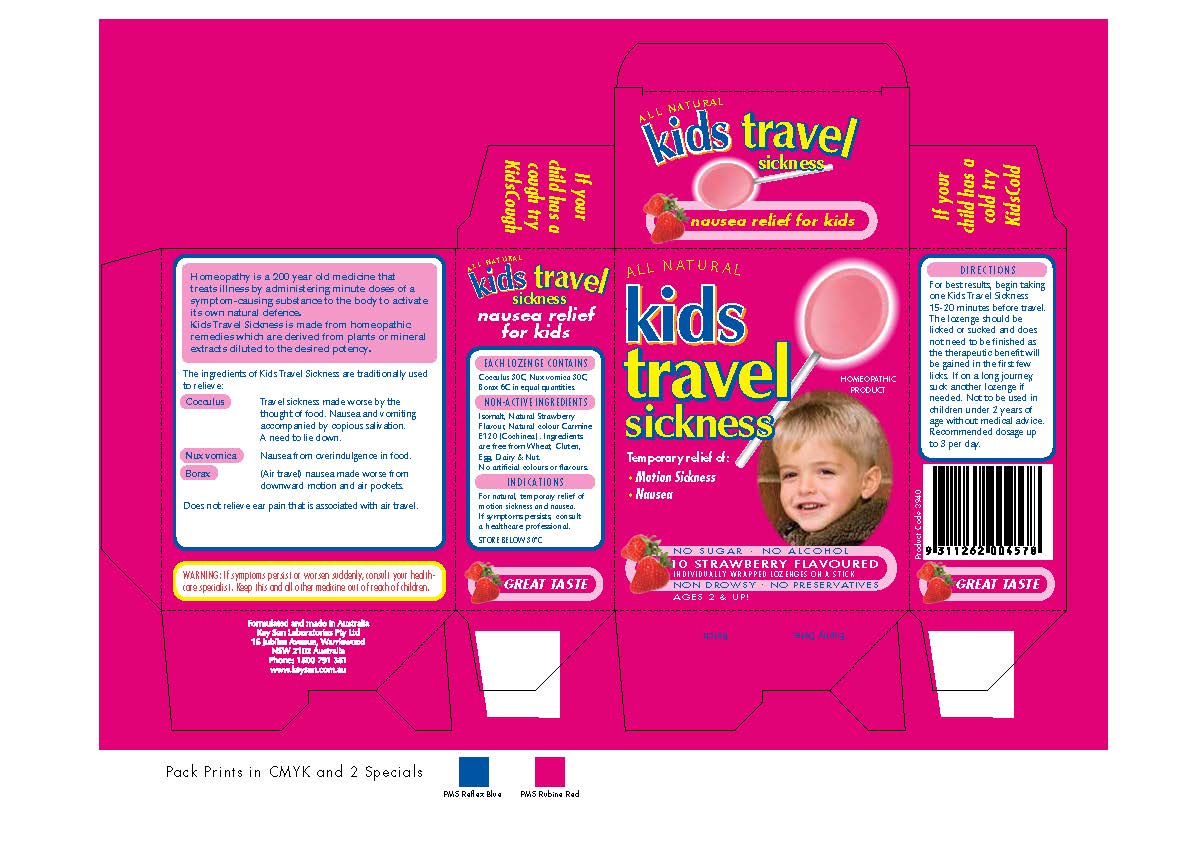 DRUG LABEL: Kids Travel Sickness
                
NDC: 64997-050 | Form: LOZENGE
Manufacturer: KEYSUN PTY. LIMITED Also Traded as KEYSUN LABORATORIES
Category: homeopathic | Type: HUMAN OTC DRUG LABEL
Date: 20140501

ACTIVE INGREDIENTS: JATEORHIZA CALUMBA ROOT 30 [hp_X]/1 1; STRYCHNOS NUX-VOMICA SEED 30 [hp_X]/1 1; SODIUM BORATE 6 [hp_X]/1 1
INACTIVE INGREDIENTS: ISOMALT

Homeopathic Drug Facts

INACTIVE INGREDIENT

Non-Active Ingredients

Isomalt, Natural Strawberry Flavour,

Natural Colour Carmine E120 (Cochineal).

ACTIVE INGREDIENT

Each Lozenge Contains

Cocculus 30C, Nux Vomica 30C,

Borax 6C in equal quantities

PURPOSE

Indications

For natural temporary relief of

motion sickness and nausea

WARNINGS

Warning: If symptoms persist or worsen suddenly, consult your health-care

specialist.

KEEP OUT OF REACH OF CHILDREN

Keep this and all other medicine out of the reach of children.

Directions

For best results, begin taking one Kids Travel Sickness

15-20 minutes before travel. The lozenge should be licked

or sucked and does not need to be finished as the

therapeutic benefit will be gained in the first few licks.

If on a long journey, suck another lozenge if needed. Not

to be used in children under 2 years of age without medical advice.

Recommended dosage up to 3 per day.

STORAGE AND HANDLING

STORE BELOW 30 C

Indications

For natural, temporary relief of motion sickness

and nausea